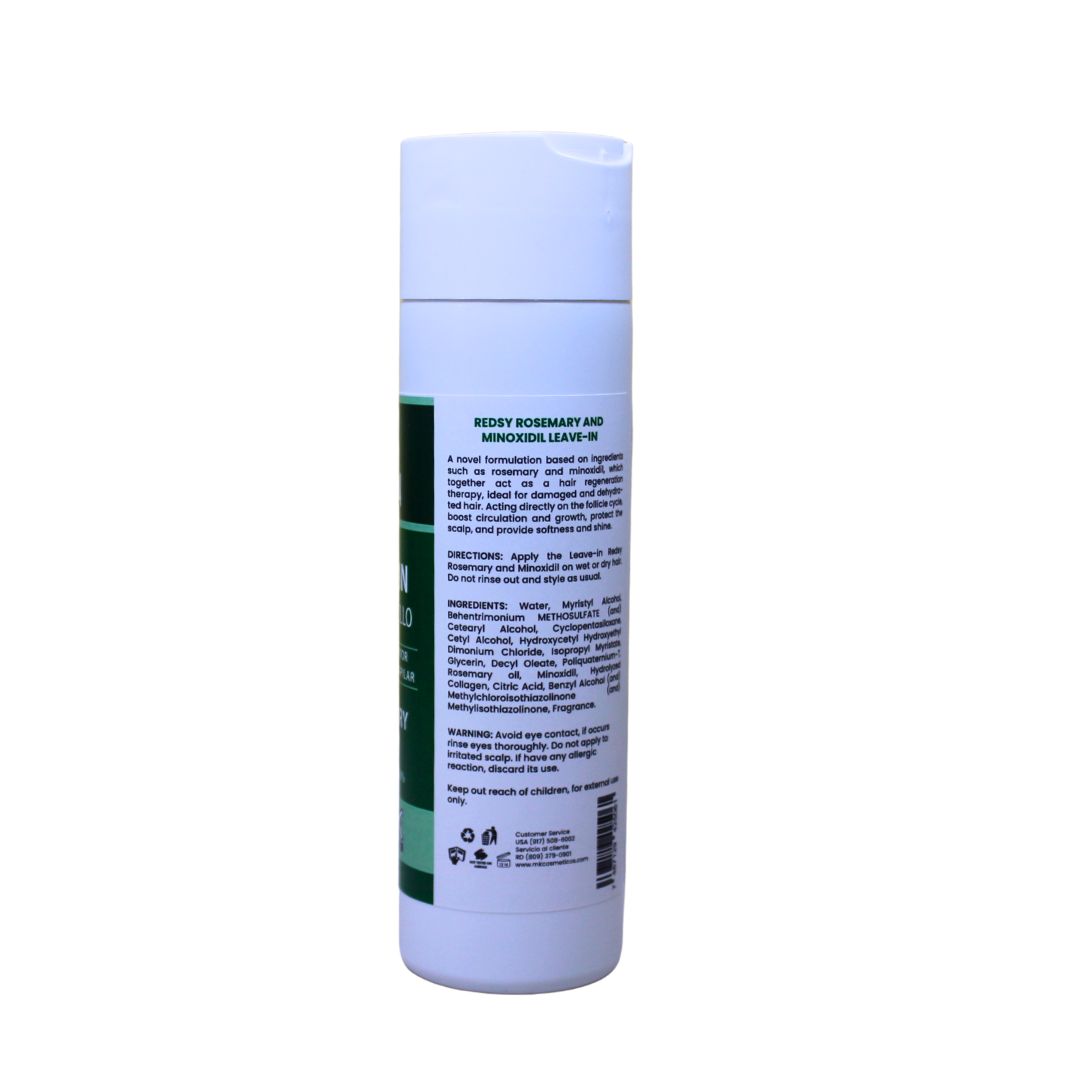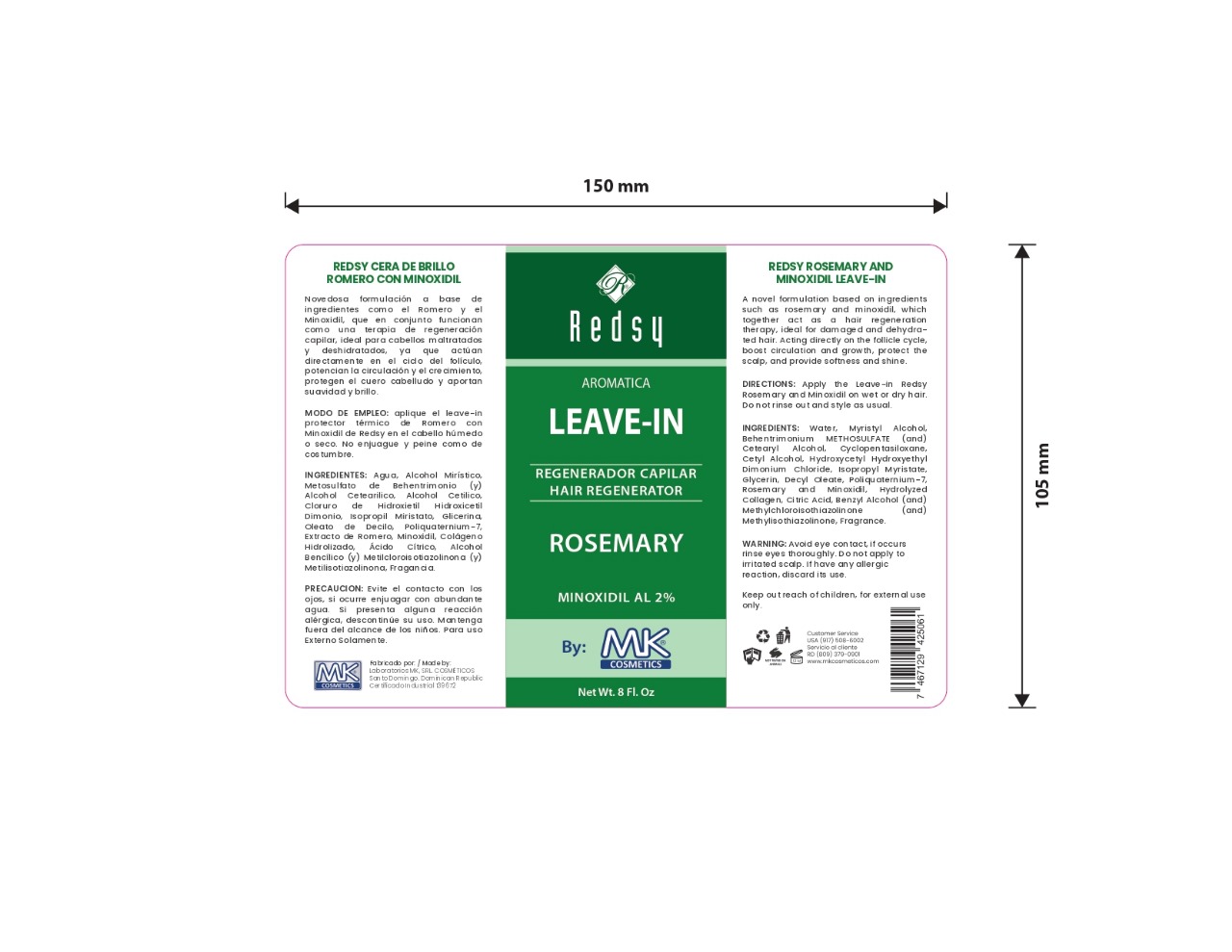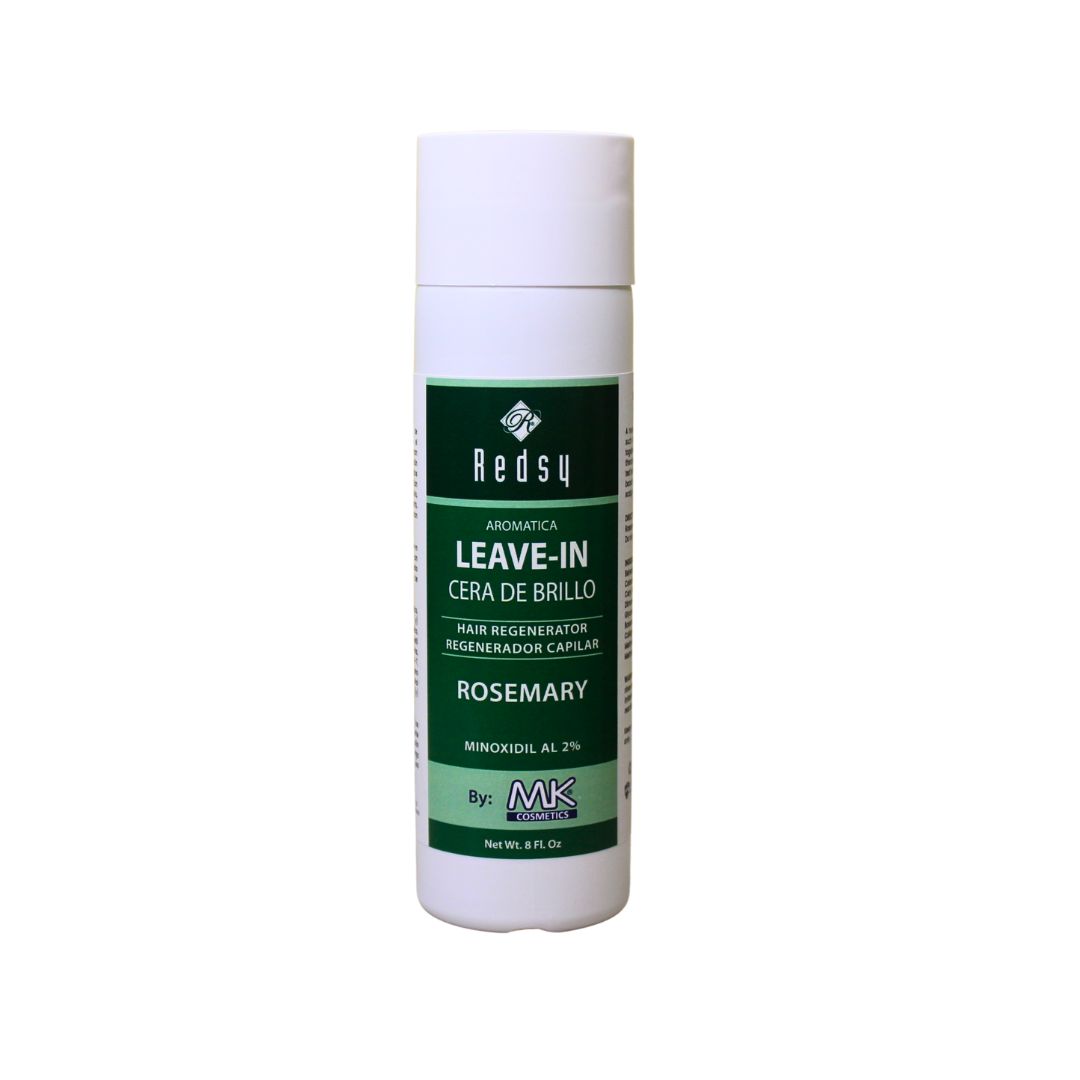 DRUG LABEL: aromatica hair leave in romero con minoxidil
NDC: 87022-016 | Form: CREAM
Manufacturer: LABORATORIO MK SRL
Category: otc | Type: HUMAN OTC DRUG LABEL
Date: 20251008

ACTIVE INGREDIENTS: MINOXIDIL 2 mg/234 mL
INACTIVE INGREDIENTS: WATER; CYCLOPENTASILOXANE; HYDROXYCETYL HYDROXYETHYL DIMONIUM CHLORIDE; ROSEMARY OIL; BEHENTRIMONIUM METHOSULFATE; MYRISTYL ALCOHOL; ISOPROPYL MYRISTATE; DECYL OLEATE; POLYQUATERNIUM-7; HYDROLYZED PORCINE COLLAGEN (ENZYMATIC; 3000 MW); CITRIC ACID; BENZYL ALCOHOL; METHYLCHLOROISOTHIAZOLINONE; METHYLISOTHIAZOLINONE; GLYCERIN; CETEARYL ALCOHOL; CETYL ALCOHOL

INDICATIONS AND USAGE

Apply the Leave-in Redsy Rosemary and Minoxidil on wet or dry hair. Do not rinse out and style as usual.

INACTIVE INGREDIENT

Water, Myristyl Alcohol, Behentrimonium METHOSULFATE (and) Cetearyl Alcohol, Cyclopentasiloxane, Cetyl Alcohol, Hydroxycetyl Hydroxyethyl Dimonium Chloride, Isopropyl Myristate, Glycerin, Decyl Oleate, Poliquaternium-7, Rosemary, Hydrolyzed Collagen, Citric Acid, Benzyl Alcohol (and) Methylchloroisothiazolinone (and) Methylisothiazolinone, Fragrance.

WARNINGS

Avoid eye contact, if occurs rinse eyes thoroughly with water. If develop any allergic reaction, discontinue its use.

INFORMATION FOR OWNERS/CAREGIVERS

Customer Service USA (917)508-6002

Customer Service RD (809)379-0900

www.mkcosmeticos.com

DOSAGE AND ADMINISTRATION

Apply the Leave-in Redsy Rosemary and Minoxidil on wet or dry hair. Do not rinse out and style as usual.

KEEP OUT OF REACH OF CHILDREN

Keep out reach of children. For external use only.

PURPOSE

Aromatica hair regenerator

PACKAGE LABEL

aromatica leave in hair regenerator rosemary with minoxidil